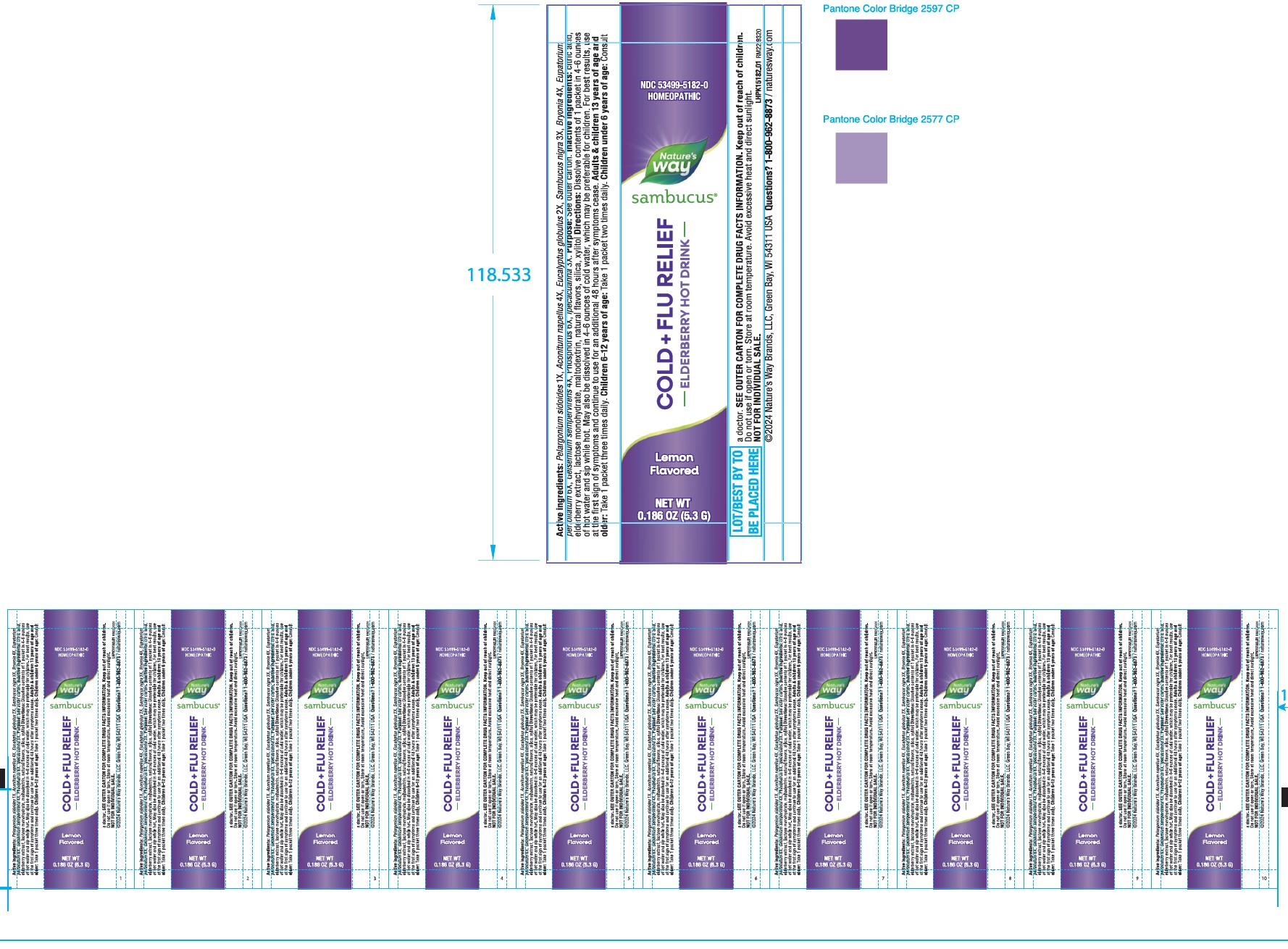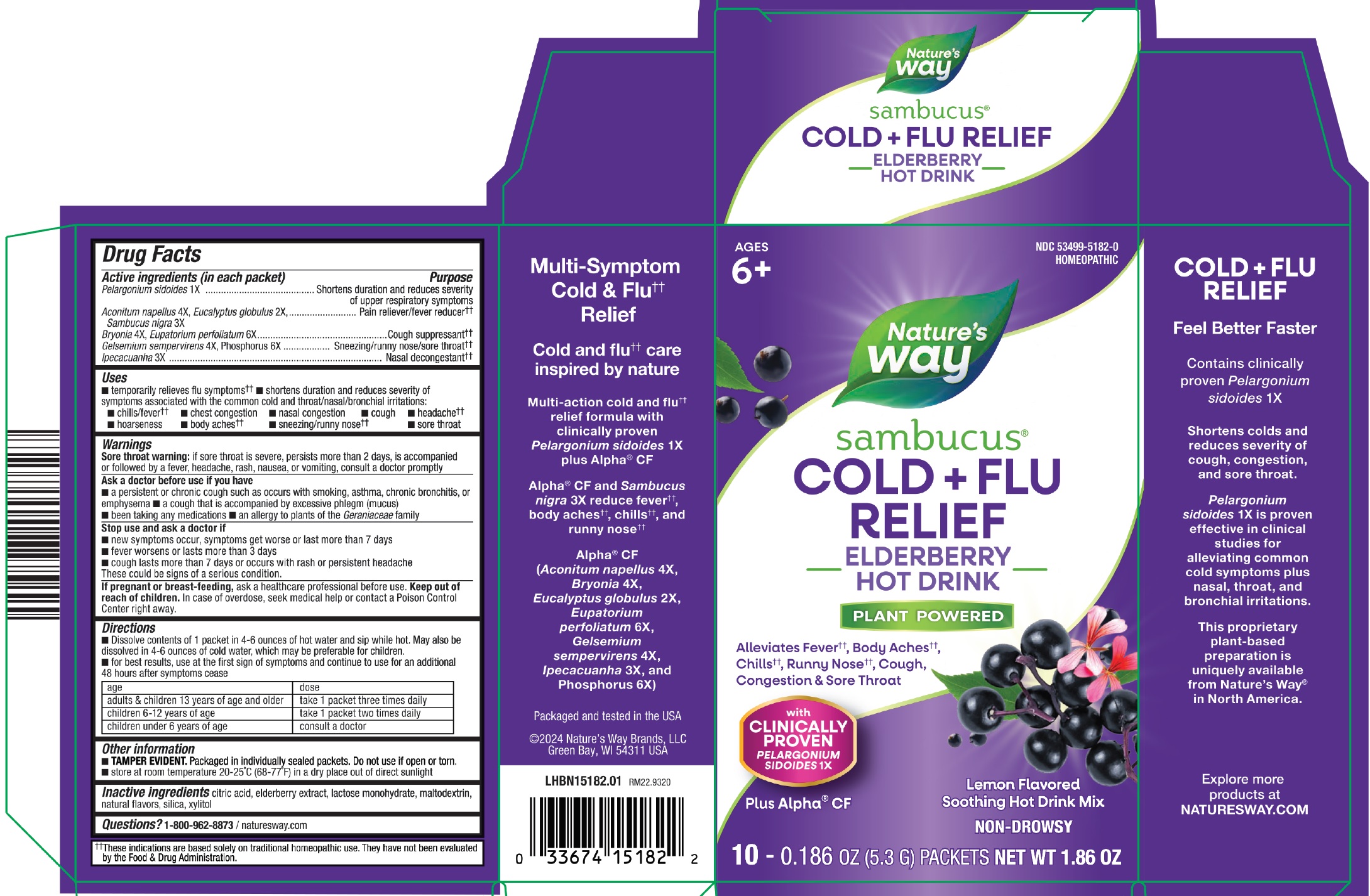 DRUG LABEL: Sambucus Cold Flu Relief Hot Drink Lemon Flavored
NDC: 80228-5182 | Form: POWDER
Manufacturer: Universal Synergetics, Inc
Category: otc | Type: HUMAN OTC DRUG LABEL
Date: 20250304

ACTIVE INGREDIENTS: PELARGONIUM SIDOIDES WHOLE 1 [hp_X]/1 g; ACONITUM NAPELLUS 4 [hp_X]/1 g; EUCALYPTUS GLOBULUS LEAF 2 [hp_X]/1 g; SAMBUCUS NIGRA FLOWERING TOP 3 [hp_X]/1 g; BRYONIA ALBA ROOT 4 [hp_X]/1 g; EUPATORIUM PERFOLIATUM FLOWERING TOP 6 [hp_X]/1 g; GELSEMIUM SEMPERVIRENS ROOT 4 [hp_X]/1 g; PHOSPHORUS 6 [hp_X]/1 g; IPECAC 3 [hp_X]/1 g
INACTIVE INGREDIENTS: CITRIC ACID MONOHYDRATE; EUROPEAN ELDERBERRY JUICE; LACTOSE MONOHYDRATE; MALTODEXTRIN; SILICON DIOXIDE; XYLITOL

Sambucus Cold + Flu Relief Hot Drink, Lemon Flavored

Active ingredients (in each packet)

Pelargonium sidoides 1 X
Aconitum napellus 4X, Eucalyptus globulus 2X,
Sambucus nigra 3X
Bryonia 4X, Eupatorium perfoliatum 6X
Gelsemium sempervirens 4X, Phosphorus 6X
Ipecacuanha 3X

Purpose

Shortens duration and reduces severity of upper respiratory symptoms
Pain reliever/fever reducer++
Cough suppressant++
Sneezing/runny nose/sore throat++
Nasal decongestant++

Uses

- temporarily relieves flu symptoms++
- shortens duration and reduces severity of symptoms associated with the common cold and throat/nasal/bronchial irritations:
- chills/fever++
- chest congestion
- nasal congestion
- cough
- headache++
- hoarseness
- body aches++
- sneezing/runny nose++
- sore throat

Warnings

Sore throat warning: if sore throat is severe, persists more than 2 days, is accompained or followed by a fever, headche, rash, nausea, or vomiting, consult a doctor promptly

Ask a doctor before use if you have

- a persistent or chronic cough such as occurs with smoking, asthma, chronic bronchitis, or emphysema
- a cough that is accompained by excessive phlegm (mucus)
- been taking any medications
- an allergy to plants of the Geraniaceae family

Stop use and ask a doctor

- new symptoms occur, symptoms get worse or last more than 7 days
- fever worsens or lasts more than 3 days
- cough lasts more than 7 days or occurs with rash or persistent headache

These could be sign of a serious condition.

If pregnant or brest-feeding,

ask a healthcare professional before use.

Keep out of reach of children.

In case of overdose, seek medical help or contact a Poison Control Center right away.

Directions

- Dissolve contents of 1 packet in 4-6 ounes of hot water and sip while hot. May also be dissolved in 4-6 ounces of water, which may be preferable for children.
- for best results, use at the first sign of symptoms and continue to use for an additional 48 hours after symptoms cease

age | dose
adults & children 13 years of age and older | take 1 packet three times daily
children 6-12 years of age | take 1 packet two times daily
children under 6 years of age | consult a doctor

Other information

- TAMPER EVIDENT.Packaged in individually sealed packets. Do not use if open or torn.
- store at room temperature 20 25°C (68-77°F) in a dry place out of direct sunlight

Inactive ingredients

citric acid, elderberry extract, lactose monohydrate, maltodextrin, natural flavours, silica, xylitol

Questions?

1-800-962-8873 / naturesway.com